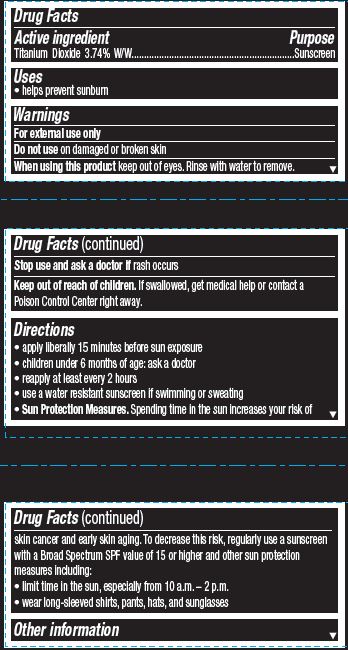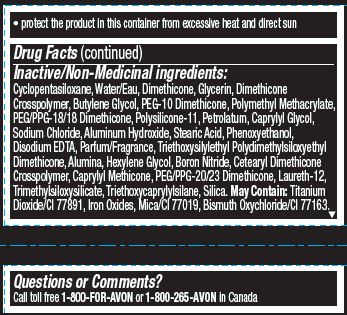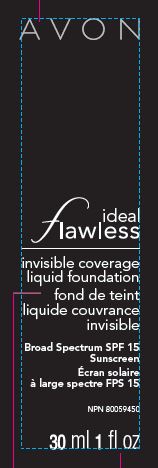 DRUG LABEL: Ideal Flawless
NDC: 10096-0330 | Form: LOTION
Manufacturer: New Avon LLC
Category: otc | Type: HUMAN OTC DRUG LABEL
Date: 20190101

ACTIVE INGREDIENTS: TITANIUM DIOXIDE 37.4 mg/1 mL
INACTIVE INGREDIENTS: WATER

Avon True Color Ideal Nude Liquid Foundation SPF 20

Active ingredient
Titanium Dioxide 3.74% W/W................................

Purpose
.................................Sunscreen

Uses
• helps prevent sunburn

Warnings
For external use only

Do not use on damaged or broken skin

When using this product keep out of eyes. Rinse with water to remove.

Stop use and ask a doctor if rash occurs

Keep out of reach of children. If swallowed, get medical help or contact a Poison Control Center right away.

Directions
• apply liberally 15 minutes before sun exposure
• children under 6 months of age: ask a doctor
• reapply at least every 2 hours
• use a water resistant sunscreen if swimming or sweating
• Sun Protection Measures. Spending time in the sun increases your risk of skin cancer and early skin aging. To decrease this risk, regularly use a sunscreen with a Broad Spectrum SPF value of 15 or higher and other sun protection measures including:
• limit time in the sun, especially from 10 a.m. – 2 p.m.
• wear long-sleeved shirts, pants, hats, and sunglasses

Other information

• protect the product in this container from excessive heat and direct sun

Inactive/Non-Medicinal Ingredients:
Cyclopentasiloxane,Water/Eau, Dimethicone, Glycerin, Dimethicone Crosspolymer, Butylene Glycol, PEG-10 Dimethicone, Polymethyl Methacrylate, PEG/PPG-18/18 Dimethicone, Polysilicone-11, Petrolatum, Caprylyl Glycol, Sodium Chloride, Aluminum Hydroxide, Stearic Acid, Phenoxyethanol, Disodium EDTA, Parfum/Fragrance, Triethoxysilylethyl Polydimethylsiloxyethyl Dimethicone, Alumina, Hexylene Glycol, Boron Nitride, Cetearyl Dimethicone Crosspolymer, Caprylyl Methicone, PEG/PPG-20/23 Dimethicone, Laureth-12, Trimethylsiloxysilicate, Triethoxycaprylylsilane, Silica. May Contain: Titanium Dioxide/CI 77891, Iron Oxides, Mica/CI 77019, Bismuth Oxychloride/CI 77163.

Questions or Comments?
Call toll free 1-800-FOR-AVON or 1-800-265-AVON in Canada